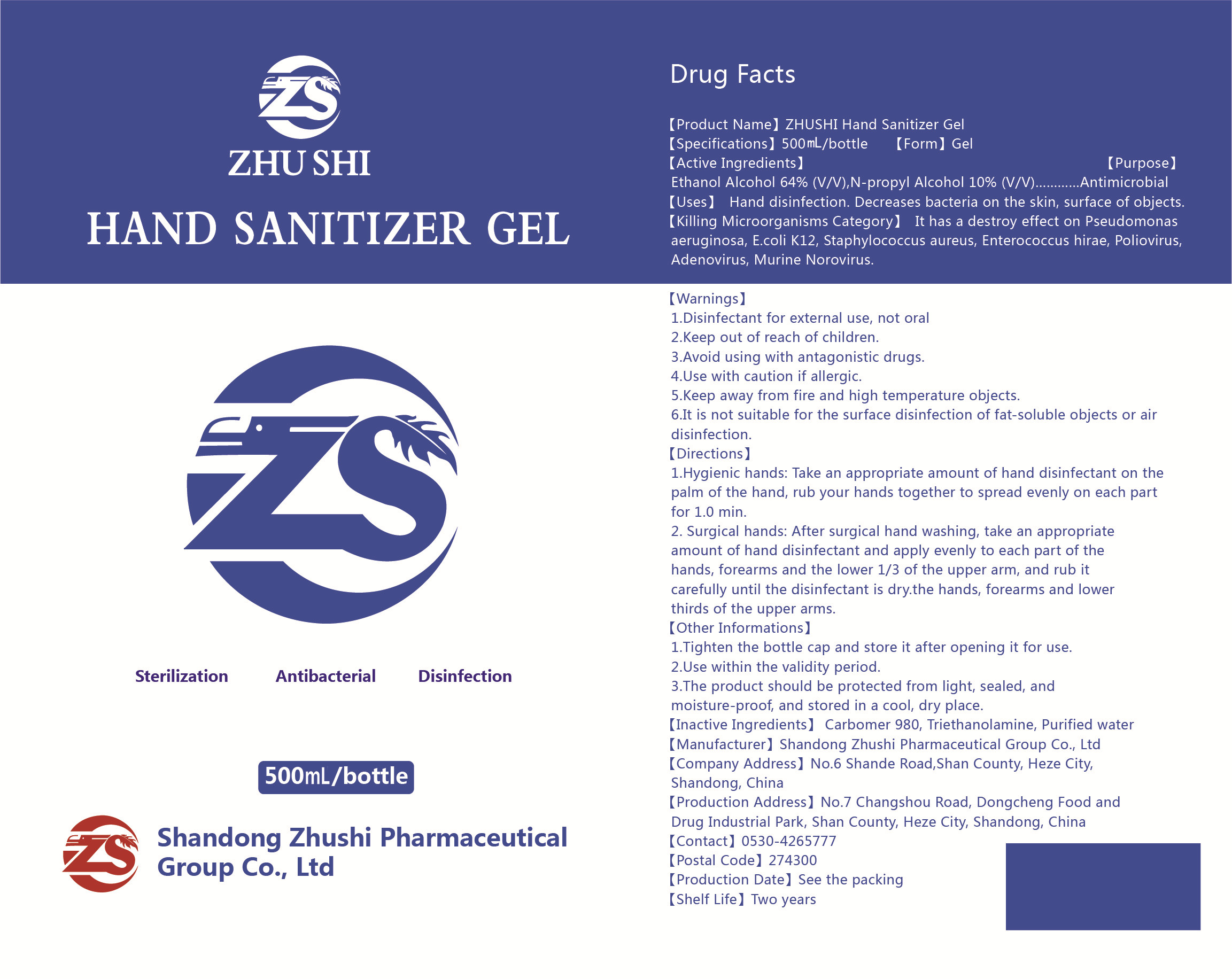 DRUG LABEL: ZHUSHI Hand sanitizer gel
NDC: 56040-011 | Form: GEL
Manufacturer: Shandong Zhushi Pharmaceutical Group Co., Ltd
Category: otc | Type: HUMAN OTC DRUG LABEL
Date: 20220310

ACTIVE INGREDIENTS: ALCOHOL 320 mL/500 mL; PROPYL ALCOHOL 100 g/500 mL
INACTIVE INGREDIENTS: TROLAMINE; WATER; CARBOMER HOMOPOLYMER TYPE C (ALLYL PENTAERYTHRITOL CROSSLINKED)

Directions

1.Hygienic hands: Take an appropriate amount of hand disinfectant on the palm of the hand, rub your hands together to spread evenly on each partfor 1.0 min.
2.Surgical hands: After surgical hand washing, take an appropriateamount of hand disinfectant and apply evenly to each part of the hands, forearms and the lower 1/3 of the upper arm, and rub it carefully until the disinfectant is dry.the hands, forearms and lower thirds of the upper arms.

Uses

Hand disinfection. Decreases bacteria on the skin, surface of objects.

ACTIVE INGREDIENT

ethanol alcohol

N-propanol

Keep out of reach of children.

PURPOSE

Antimicrobial

WARNINGS

1.Disinfectant for external use, not oral
2.Keep out of reach of children.
3.Avoid using with antagonistic drugs.
4.Use with caution if allergic.
5.Keep away from fire and high temperature objects.
6.It is not suitable for the surface disinfection of fat-soluble objects or airdisinfection.

STORAGE AND HANDLING

1.Tighten the bottle cap and store it after opening it for use.
2.Use within the validity period.
3.The product should be protected from light, sealed, andmoisture-proof, and stored in a cool, dry place.